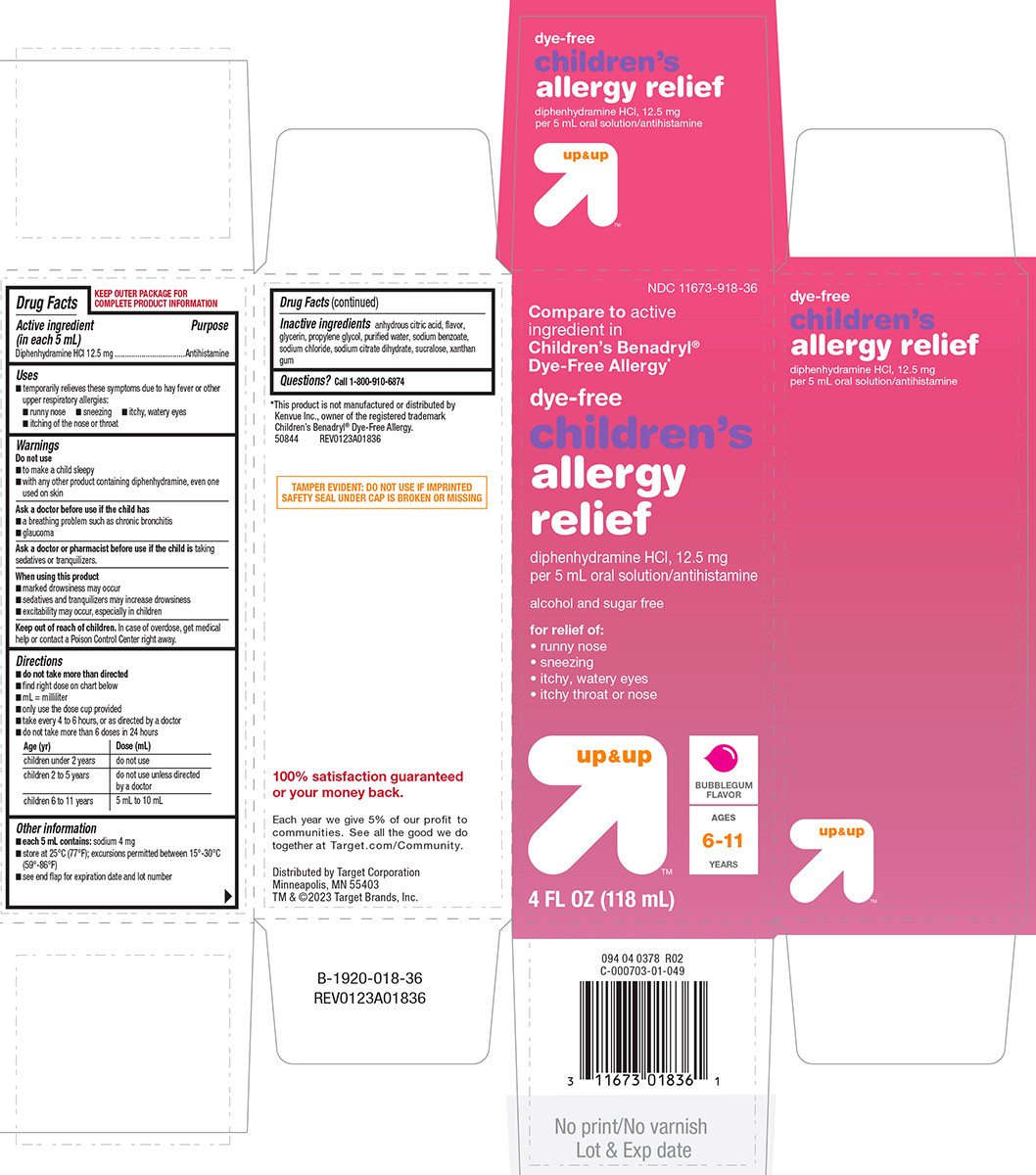 DRUG LABEL: childrens allergy relief
NDC: 11673-918 | Form: SOLUTION
Manufacturer: Target Corporation
Category: otc | Type: HUMAN OTC DRUG LABEL
Date: 20250428

ACTIVE INGREDIENTS: DIPHENHYDRAMINE HYDROCHLORIDE 12.5 mg/5 mL
INACTIVE INGREDIENTS: ANHYDROUS CITRIC ACID; GLYCERIN; PROPYLENE GLYCOL; WATER; SODIUM BENZOATE; SODIUM CHLORIDE; TRISODIUM CITRATE DIHYDRATE; SUCRALOSE; XANTHAN GUM

Target 44-018-Liquid-Delisted

Active ingredient (in each 5 mL)

Diphenhydramine HCl 12.5 mg

Purpose

Antihistamine

Uses

- temporarily relieves these symptoms due to hay fever or other upper respiratory allergies:
  - runny nose
  - itchy, watery eyes
  - sneezing
  - itching of the nose or throat

Warnings

Do not use

- to make a child sleepy
- with any other product containing diphenhydramine, even one used on skin

Ask a doctor before use if the child has

- a breathing problem such as chronic bronchitis
- glaucoma

Ask a doctor or pharmacist before use if the child is

taking sedatives or tranquilizers.

When using this product

- marked drowsiness may occur
- sedatives and tranquilizers may increase drowsiness
- excitability may occur, especially in children

Keep out of reach of children.

In case of overdose, get medical help or contact a Poison Control Center right away.

Directions

- do not take more than directed
- find right dose on chart below
- mL = milliliter
- only use the dose cup provided
- take every 4 to 6 hours, or as directed by a doctor
- do not take more than 6 doses in 24 hours

Age (yr) | Dose (mL)
children under 2 years | do not use
children 2 to 5 years | do not use unless directed by a doctor
children 6 to 11 years | 5 mL to 10 mL

Other information

- each 5 mL contains: sodium 4 mg
- store at 25ºC (77ºF); excursions permitted between 15º-30ºC (59º-86ºF)
- see end flap for expiration date and lot number

Inactive ingredients

anhydrous citric acid, flavor, glycerin, propylene glycol, purified water, sodium benzoate, sodium chloride, sodium citrate dihydrate, sucralose, xanthan gum

Questions or comments?

Call 1-800-910-6874

Principal Display Panel

NDC 11673-918-36

Compare to active
ingredient in
Children's Benadryl®
Dye-Free Allergy*

dye-free

children's
allergy
relief

diphenhydramine HCl, 12.5 mg
per 5 mL oral solution/antihistamine

alcohol and sugar free

for relief of:
• runny nose
• sneezing
• itchy, watery eyes
• itchy throat or nose

up & up™

BUBBLEGUM
FLAVOR

AGES
6-11
YEARS

4 FL OZ (118 mL)

*This product is not manufactured or distributed by
Kenvue Inc., owner of the registered trademark
Children’s Benadryl® Dye-Free Allergy.

50844 REV0123A01836

TAMPER EVIDENT: DO NOT USE IF IMPRINTED
SAFETY SEAL UNDER CAP IS BROKEN OR MISSING

100% satisfaction guaranteed
or your money back.

Each year we give 5% of our profit to
communities. See all the good we do
together at Target.com/Community.

Distributed by Target Corporation
Minneapolis, MN 55403
TM & ©2023 Target Brands, Inc.

Target 44-018